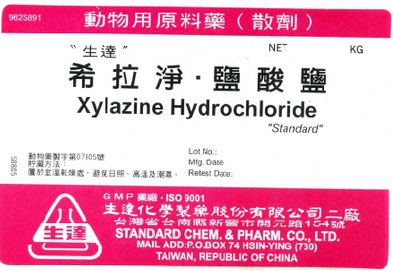 DRUG LABEL: Xylazine Hydrochloride
NDC: 63537-0091 | Form: POWDER
Manufacturer: Standard Chem. & Pharm. Co., Ltd.
Category: other | Type: BULK INGREDIENT - ANIMAL DRUG
Date: 20220518

ACTIVE INGREDIENTS: XYLAZINE HYDROCHLORIDE 1 kg/1 kg

Xylazine Hydrochloride